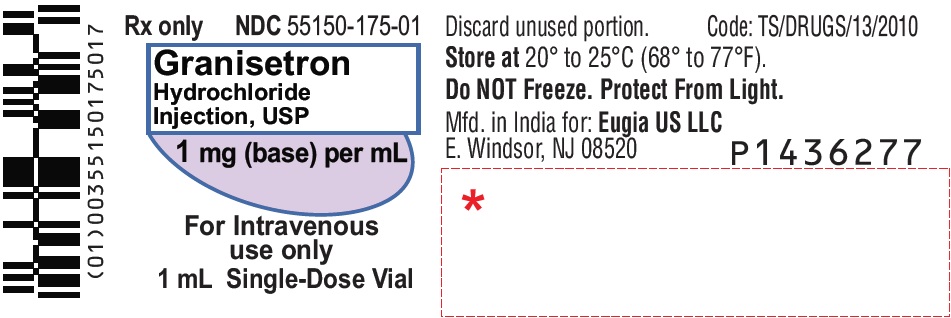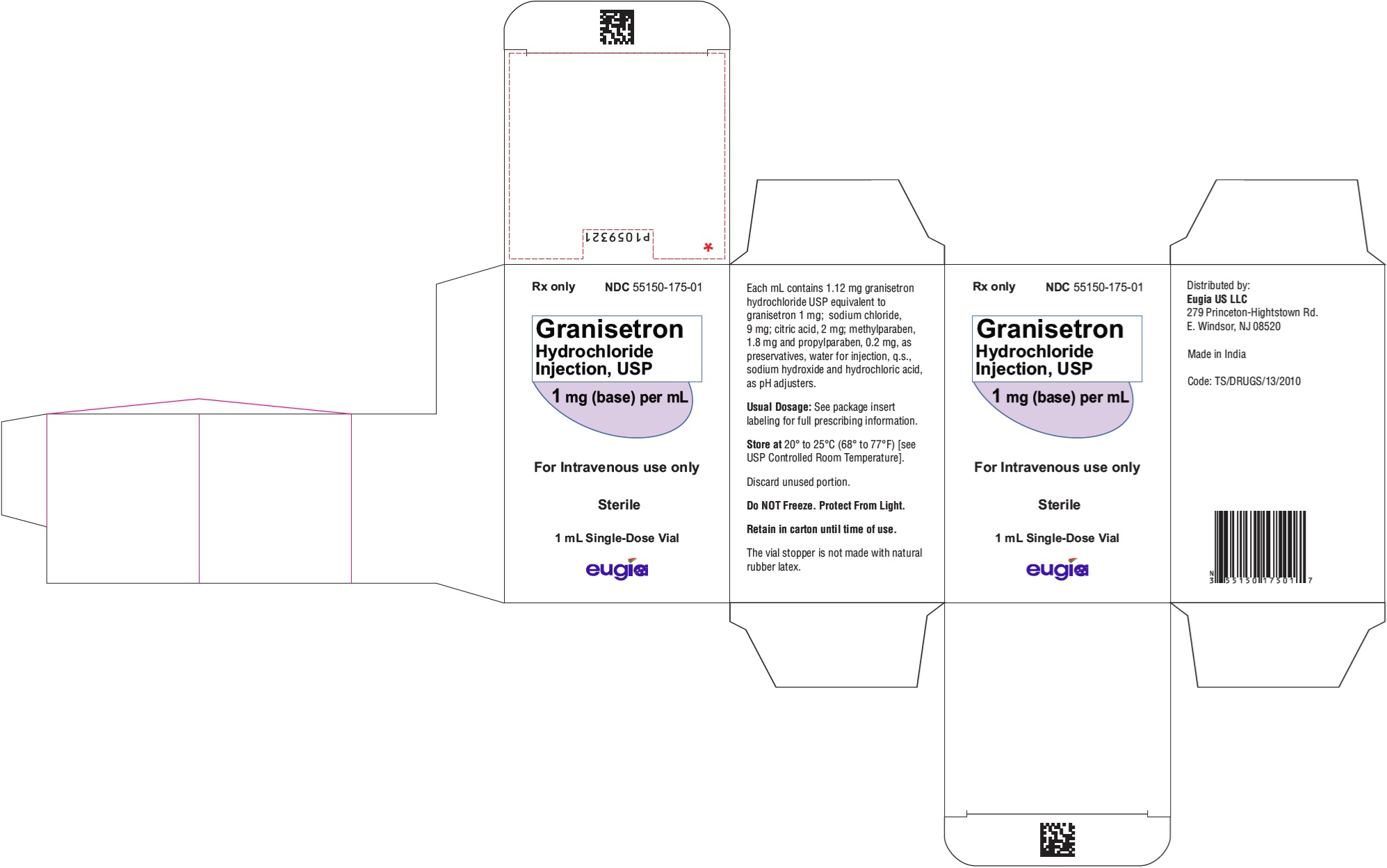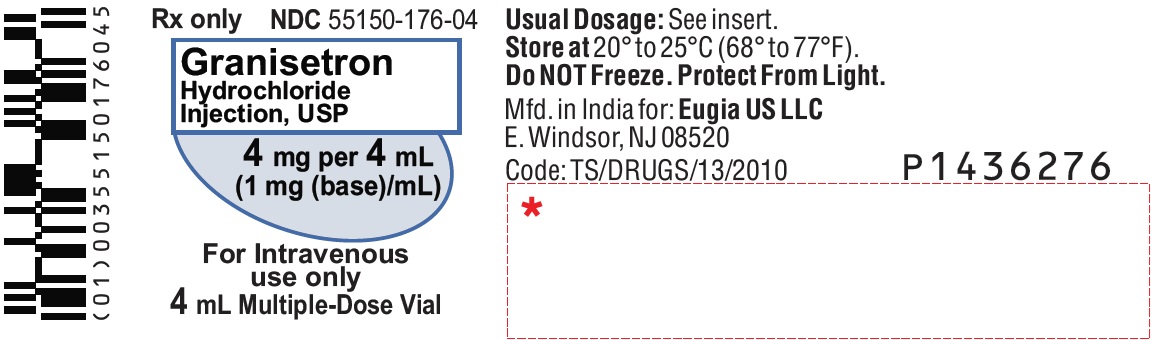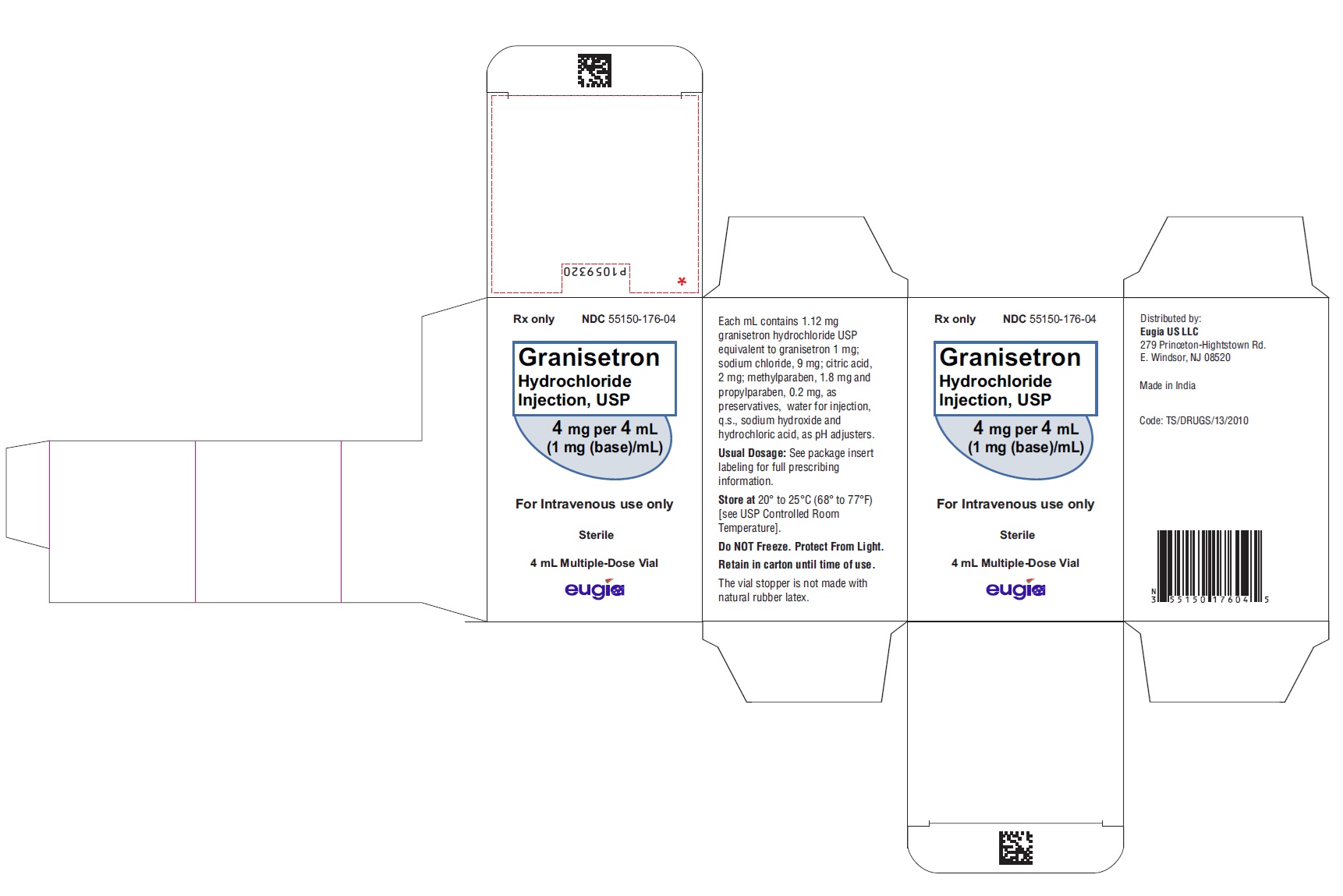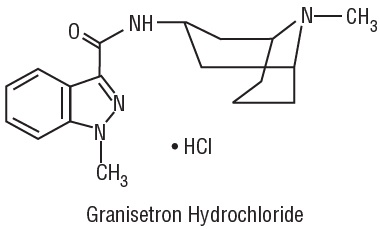 DRUG LABEL: Granisetron Hydrochloride
NDC: 55150-175 | Form: INJECTION, SOLUTION
Manufacturer: Eugia US LLC
Category: prescription | Type: Human Prescription Drug Label
Date: 20250424

ACTIVE INGREDIENTS: GRANISETRON HYDROCHLORIDE 1 mg/1 mL
INACTIVE INGREDIENTS: SODIUM CHLORIDE; CITRIC ACID MONOHYDRATE; METHYLPARABEN; PROPYLPARABEN; WATER; SODIUM HYDROXIDE; HYDROCHLORIC ACID

HIGHLIGHTS OF PRESCRIBING INFORMATION

These highlights do not include all the information needed to use GRANISETRON HYDROCHLORIDE INJECTION safely and effectively. See full prescribing information for GRANISETRON HYDROCHLORIDE INJECTION.
GRANISETRON HYDROCHLORIDE injection, for intravenous use
Initial U.S. Approval: 1993

1 INDICATIONS AND USAGE

Granisetron hydrochloride injection, is a serotonin-3 (5-HT3) receptor antagonist indicated for:

- Prevention of nausea and/or vomiting associated with initial and repeat courses of emetogenic cancer therapy, including high-dose cisplatin. (1)
- Prevention and treatment of postoperative nausea and vomiting in adults. (1)

2 DOSAGE AND ADMINISTRATION

Prevention of chemotherapy-induced nausea and vomiting (2.1):

- Recommended dosage is 10 mcg/kg intravenously within 30 minutes before initiation of chemotherapy
- Pediatric patients (2 to 16 years): Recommended dosage is 10 mcg/kg

Prevention of postoperative nausea and vomiting (2.2):

- Recommended dosage is 1 mg, undiluted, administered intravenously over 30 seconds, before anesthetic induction or immediately before reversal of anesthesia.

Treatment of postoperative nausea and vomiting (2.2):

- Recommended dosage is 1 mg, undiluted, administered intravenously over 30 seconds.

3 DOSAGE FORMS AND STRENGTHS

- Injection 1 mg/mL (free base). (3)

4 CONTRAINDICATIONS

- Hypersensitivity to granisetron or to any of its components. (4)

5 WARNINGS AND PRECAUTIONS

- Granisetron hydrochloride does not stimulate gastric or intestinal peristalsis and should not be used instead of nasogastric suction. (5.1)
- QT prolongation has been reported with granisetron hydrochloride. Use with caution in patients with pre-existing arrhythmias or cardiac conduction disorders. (5.2)
- Hypersensitivity reactions, such as anaphylaxis, shortness of breath, hypotension, and urticaria, may occur in patients with known hypersensitivity to other selective 5-HT3 receptor antagonists. (5.3)
- Serotonin syndrome has been reported with granisetron products, alone but particularly with concomitant use of serotonergic drugs. (5.4)

6 ADVERSE REACTIONS

Most common adverse reactions:

- Chemotherapy-induced nausea and vomiting (≥ 3%): Headache, and constipation (6.1)
- Postoperative nausea and vomiting (≥ 2%): Pain, headache, fever, abdominal pain and hepatic enzymes increased (6.1)

To report SUSPECTED ADVERSE REACTIONS, contact Eugia US LLC at 1-866-850-2876 or FDA at 1-800-FDA-1088 or www.fda.gov/medwatch.

7 DRUG INTERACTIONS

- Granisetron hydrochloride injection has been administered safely with benzodiazepines, neuroleptics, and anti-ulcer medications. (7)
- Does not appear to interact with emetogenic cancer chemotherapies. (7)
- Inducers or inhibitors of CYP450 enzymes may change the clearance and therefore the half-life of granisetron. (7)
- Coadministration of granisetron hydrochloride with drugs known to prolong the QT interval and/or are arrhythmogenic may result in clinical consequences. (7)

8 USE IN SPECIFIC POPULATIONS

- Pregnancy: Use only if clearly needed. (8.1)
- Nursing mothers: Caution should be exercised when administered to a nursing woman. (8.3)
- Pediatric use: Safety and efficacy in pediatric patients have not been established for use in postoperative nausea and vomiting. (8.4)
- Geriatric use: No differences in responses between the elderly and younger patients were observed in reported clinical experience. (8.5)

FULL PRESCRIBING INFORMATION

1 INDICATIONS AND USAGE

Granisetron hydrochloride injection, is a serotonin-3 (5-HT3) receptor antagonist indicated for:

- The prevention of nausea and/or vomiting associated with initial and repeat courses of emetogenic cancer therapy, including high-dose cisplatin.
- The prevention and treatment of postoperative nausea and vomiting in adults. As with other antiemetics, routine prophylaxis is not recommended in patients in whom there is little expectation that nausea and/or vomiting will occur postoperatively. In patients where nausea and/or vomiting must be avoided during the postoperative period, granisetron hydrochloride injection is recommended even where the incidence of postoperative nausea and/or vomiting is low.

2 DOSAGE AND ADMINISTRATION

2.1 Prevention of Chemotherapy-Induced Nausea and Vomiting

Adult Patients
The recommended dosage for granisetron hydrochloride injection, is 10 mcg/kg administered intravenously within 30 minutes before initiation of chemotherapy, and only on the day(s) chemotherapy is given.
Infusion Preparation
Granisetron hydrochloride injection, may be administered intravenously either undiluted over 30 seconds, or diluted with 0.9% Sodium Chloride or 5% Dextrose and infused over 5 minutes.
Stability
Intravenous infusion of granisetron hydrochloride injection, should be prepared at the time of administration. However, granisetron hydrochloride injection, has been shown to be stable for at least 24 hours when diluted in 0.9% Sodium Chloride or 5% Dextrose and stored at room temperature under normal lighting conditions.
As a general precaution, granisetron hydrochloride injection, should not be mixed in solution with other drugs. Parenteral drug products should be inspected visually for particulate matter and discoloration before administration whenever solution and container permit.
Pediatric Patients

The recommended dose in pediatric patients 2 to 16 years of age is 10 mcg/kg [see Clinical Studies (14)]. Pediatric patients under 2 years of age have not been studied.

2.2 Prevention and Treatment of Postoperative Nausea and Vomiting

Adult Patients
The recommended dosage for prevention of postoperative nausea and vomiting is 1 mg of granisetron hydrochloride injection, undiluted, administered intravenously over 30 seconds, before induction of anesthesia or immediately before reversal of anesthesia.
The recommended dosage for the treatment of nausea and/or vomiting after surgery is 1 mg of granisetron hydrochloride injection, undiluted, administered intravenously over 30 seconds.

3 DOSAGE FORMS AND STRENGTHS

Single-Dose Vials for Injection: 1 mg/mL
Multiple-Dose Vials for Injection: 4 mg/4 mL

4 CONTRAINDICATIONS

Granisetron hydrochloride injection is contraindicated in patients with known hypersensitivity (e.g., anaphylaxis, shortness of breath, hypotension, urticaria) to the drug or to any of its components.

5 WARNINGS AND PRECAUTIONS

5.1 Gastric or Intestinal Peristalsis

Granisetron hydrochloride is not a drug that stimulates gastric or intestinal peristalsis. It should not be used instead of nasogastric suction. The use of granisetron hydrochloride in patients following abdominal surgery or in patients with chemotherapy-induced nausea and vomiting may mask a progressive ileus and/or gastric distention.

5.2 Cardiovascular Events

An adequate QT assessment has not been conducted, but QT prolongation has been reported with granisetron hydrochloride. Therefore, granisetron hydrochloride should be used with caution in patients with pre-existing arrhythmias or cardiac conduction disorders, as this might lead to clinical consequences. Patients with cardiac disease, on cardio-toxic chemotherapy, with concomitant electrolyte abnormalities and/or on concomitant medications that prolong the QT interval are particularly at risk.

5.3 Hypersensitivity Reactions

Hypersensitivity reactions (e.g., anaphylaxis, shortness of breath, hypotension, urticaria) may occur in patients who have exhibited hypersensitivity to other selective 5-HT3 receptor antagonists.

5.4 Serotonin Syndrome

The development of serotonin syndrome has been reported with 5-HT3 receptor antagonists. Most reports have been associated with concomitant use of serotonergic drugs (e.g., selective serotonin reuptake inhibitors (SSRIs), serotonin and norepinephrine reuptake inhibitors (SNRIs), monoamine oxidase inhibitors, mirtazapine, fentanyl, lithium, tramadol, and intravenous methylene blue). Some of the reported cases were fatal. Serotonin syndrome occurring with overdose of another 5-HT3 receptor antagonist alone has also been reported. The majority of reports of serotonin syndrome related to 5-HT3 receptor antagonist use occurred in a post-anesthesia care unit or an infusion center.
Symptoms associated with serotonin syndrome may include the following combination of signs and symptoms: mental status changes (e.g., agitation, hallucinations, delirium, and coma), autonomic instability (e.g., tachycardia, labile blood pressure, dizziness, diaphoresis, flushing, hyperthermia), neuromuscular symptoms (e.g., tremor, rigidity, myoclonus, hyperreflexia, incoordination), seizures, with or without gastrointestinal symptoms (e.g., nausea, vomiting, diarrhea). Patients should be monitored for the emergence of serotonin syndrome, especially with concomitant use of granisetron and other serotonergic drugs. If symptoms of serotonin syndrome occur, discontinue granisetron and initiate supportive treatment. Patients should be informed of the increased risk of serotonin syndrome, especially if granisetron is used concomitantly with other serotonergic drugs [see Drug Interactions (7), Patient Counseling Information (17.1)].

6 ADVERSE REACTIONS

QT prolongation has been reported with granisetron hydrochloride [see Warnings and Precautions (5.2) and Drug Interactions (7)].

6.1 Clinical Trials Experience

Because clinical trials are conducted under widely varying conditions, adverse reaction rates observed in the clinical trials of a drug cannot be directly compared to rates in the clinical trials of another drug and may not reflect the rates observed in patients.
Chemotherapy-Induced Nausea and Vomiting
The following have been reported during controlled clinical trials or in the routine management of patients. The percentage figures are based on clinical trial experience only. Table 1 gives the comparative frequencies of the two most commonly reported adverse reactions (≥ 3%) in patients receiving granisetron hydrochloride injection, in single-day chemotherapy trials. These patients received chemotherapy, primarily cisplatin, and intravenous fluids during the 24-hour period following granisetron hydrochloride injection administration. Reactions were generally recorded over seven days post-granisetron hydrochloride injection administration.

Table 1 Principal Adverse Reactions in Clinical Trials — Single-Day Chemotherapy
Percent of Patients With Reaction
 | Granisetron Hydrochloride Injection 40 mcg/kg (n = 1268) | Comparator^1 (n = 422)
Headache Constipation | 14% 3% | 6% 3%
^1 Metoclopramide/dexamethasone and phenothiazines/dexamethasone.

Additional adverse events reported in clinical trials were asthenia, somnolence and diarrhea.
In over 3,000 patients receiving granisetron hydrochloride injection (2 to 160 mcg/kg) in single-day and multiple-day clinical trials with emetogenic cancer therapies, adverse events, other than those adverse reactions listed in Table 1, were observed; attribution of many of these events to granisetron hydrochloride is uncertain.
Hepatic: In comparative trials, mainly with cisplatin regimens, elevations of AST and ALT (> 2 times the upper limit of normal) following administration of granisetron hydrochloride injection occurred in 2.8% and 3.3% of patients, respectively. These frequencies were not significantly different from those seen with comparators (AST: 2.1%; ALT: 2.4%).
Cardiovascular: Hypertension (2%); hypotension, arrhythmias such as sinus bradycardia, atrial fibrillation, varying degrees of A-V block, ventricular ectopy including non-sustained tachycardia, and ECG abnormalities have been observed rarely.
Central Nervous System: Agitation, anxiety, CNS stimulation and insomnia were seen in less than 2% of patients. Extrapyramidal syndrome occurred rarely and only in the presence of other drugs associated with this syndrome.
Hypersensitivity: Rare cases of hypersensitivity reactions, sometimes severe (e.g., anaphylaxis, shortness of breath, hypotension, urticaria) have been reported.
Other: Fever (3%), taste disorder (2%), skin rashes (1%). In multiple-day comparative studies, fever occurred more frequently with granisetron hydrochloride injection (8.6%) than with comparative drugs (3.4%, P < 0.014), which usually included dexamethasone.
Postoperative Nausea and Vomiting
The adverse reactions listed in Table 2 were reported in ≥ 2% of adults receiving granisetron hydrochloride injection 1 mg during controlled clinical trials.

Table 2 Adverse Reactions in Controlled Clinical Trials in Postoperative Nausea and Vomiting (Reported in ≥ 2% of Adults Receiving Granisetron Hydrochloride Injection 1 mg)
Percent of Patients With Reaction
 | Granisetron Hydrochloride Injection 1 mg (n=267) | Placebo (n=266)
Pain | 10.1 | 8.3
Headache | 8.6 | 7.1
Fever | 7.9 | 4.5
Abdominal Pain | 6 | 6
Hepatic Enzymes Increased | 5.6 | 4.1
Dizziness | 4.1 | 3.4
Diarrhea | 3.4 | 1.1
Flatulence | 3 | 3
Dyspepsia | 3 | 1.9
Oliguria | 2.2 | 1.5
Coughing | 2.2 | 1.1

Additional adverse events reported in clinical trials were constipation, anemia, insomnia, bradycardia, leukocytosis, anxiety, hypotension, infection, hypertension, and urinary tract infection.
In a clinical study conducted in Japan, the types of adverse events differed notably from those reported above in Table 2. The adverse events in the Japanese study that occurred in ≥ 2% of patients and were more frequent with granisetron hydrochloride injection 1 mg than with placebo were: fever (56% to 50%), sputum increased (2.7% to 1.7%), and dermatitis (2.7% to 0%).

6.2 Postmarketing Experience

The following adverse reactions have been identified during post approval use of granisetron hydrochloride. Because these reactions are reported voluntarily from a population of uncertain size, it is not always possible to reliably estimate their frequency or establish a causal relationship to granisetron hydrochloride exposure.
QT prolongation has been reported with granisetron hydrochloride [see Warnings and Precautions (5.2) and Drug Interactions (7)].

7 DRUG INTERACTIONS

Granisetron does not induce or inhibit the cytochrome P-450 drug-metabolizing enzyme system in vitro. There have been no definitive drug-drug interaction studies to examine pharmacokinetic or pharmacodynamic interaction with other drugs; however, in humans, granisetron hydrochloride injection has been safely administered with drugs representing benzodiazepines, neuroleptics and anti-ulcer medications commonly prescribed with antiemetic treatments. Granisetron hydrochloride injection also does not appear to interact with emetogenic cancer chemotherapies. Because granisetron is metabolized by hepatic cytochrome P-450 drug-metabolizing enzymes, inducers or inhibitors of these enzymes may change the clearance and, hence, the half-life of granisetron. No specific interaction studies have been conducted in anesthetized patients. In addition, the activity of the cytochrome P-450 subfamily 3A4 (involved in the metabolism of some of the main narcotic analgesic agents) is not modified by granisetron hydrochloride in vitro.
In in vitro human microsomal studies, ketoconazole inhibited ring oxidation of granisetron hydrochloride. However, the clinical significance of in vivo pharmacokinetic interactions with ketoconazole is not known. In a human pharmacokinetic study, hepatic enzyme induction with phenobarbital resulted in a 25% increase in total plasma clearance of intravenous granisetron hydrochloride. The clinical significance of this change is not known.
QT prolongation has been reported with granisetron hydrochloride. Use of granisetron hydrochloride in patients concurrently treated with drugs known to prolong the QT interval and/or are arrhythmogenic may result in clinical consequences.
Serotonin syndrome (including altered mental status, autonomic instability, and neuromuscular symptoms) has been described following the concomitant use of 5-HT3 receptor antagonists and other serotonergic drugs, including selective serotonin reuptake inhibitors (SSRIs) and serotonin and norepinephrine reuptake inhibitors (SNRIs) [see Warnings and Precautions (5.4)].

8 USE IN SPECIFIC POPULATIONS

8.1 Pregnancy

Teratogenic Effects

Reproduction studies have been performed in pregnant rats at intravenous doses up to 9 mg/kg/day (54 mg/m^2/day, 146 times the recommended human dose based on body surface area) and pregnant rabbits at intravenous doses up to 3 mg/kg/day (35.4 mg/m^2/day, 96 times the recommended human dose based on body surface area) and have revealed no evidence of impaired fertility or harm to the fetus due to granisetron. There are, however, no adequate and well-controlled studies in pregnant women. Because animal reproduction studies are not always predictive of human response, this drug should be used during pregnancy only if clearly needed.

8.3 Nursing Mothers

It is not known whether granisetron is excreted in human milk. Because many drugs are excreted in human milk, caution should be exercised when granisetron hydrochloride injection is administered to a nursing woman.

8.4 Pediatric Use

Chemotherapy-Induced Nausea and Vomiting
[See Dosage and Administration (2)] for use in chemotherapy-induced nausea and vomiting in pediatric patients 2 to 16 years of age. Safety and effectiveness in pediatric patients under 2 years of age have not been established.
Postoperative Nausea and Vomiting
Safety and efficacy have not been established in pediatric patients for the prevention of postoperative nausea and vomiting (PONV). Granisetron has been evaluated in a pediatric patient clinical trial for use in the prevention of PONV. Due to the lack of efficacy and the QT prolongation observed in this trial, use of granisetron for the prevention of PONV in children is not recommended. The trial was a prospective, multicenter, randomized, double-blind, parallel-group trial that evaluated 157 children aged 2 to 16 years who were undergoing elective surgery for tonsillectomy or adenotonsillectomy. The purpose of the trial was to assess two dose levels (20 mcg/kg and 40 mcg/kg) of intravenous granisetron in the prevention of PONV. There was no active comparator or placebo. The primary endpoint was total control of nausea and vomiting (defined as no nausea, vomiting/retching, or use of rescue medication) in the 24 hours following surgery. Efficacy was not established due to lack of a dose response.
The trial also included standard 12 lead ECGs performed pre-dose and after the induction of anesthesia. ECGs were repeated at the end of surgery after the administration of granisetron and just prior to reversal of anesthesia. QT prolongation was seen at both dose levels. Five patients in this trial experienced an increase of ≥ 60 msec in QTcF. In addition, there were two patients whose QTcF was ≥ 500 msec. Interpretation of the QTcF prolongation was confounded by multiple factors, including the use of concomitant medication and the lack of either a placebo or active control. A thorough QT trial in adults has not been performed.
Other adverse events that occurred in the study included: vomiting (5 to 8%), post-procedural hemorrhage (3 to 5%), and dehydration (0 to 5%).
Pediatric patients under 2 years of age have not been studied.

8.5 Geriatric Use

During chemotherapy clinical trials, 713 patients 65 years of age or older received granisetron hydrochloride injection. The safety and effectiveness were similar in patients of various ages.
During postoperative nausea and vomiting clinical trials, 168 patients 65 years of age or older, of which 47 were 75 years of age or older, received granisetron hydrochloride injection. Clinical studies of granisetron hydrochloride injection did not include sufficient numbers of subjects aged 65 years and over to determine whether they respond differently from younger subjects. Other reported clinical experience has not identified differences in responses between the elderly and younger patients.

10 OVERDOSAGE

There is no specific antidote for granisetron hydrochloride injection overdosage. In case of overdosage, symptomatic treatment should be given. Overdosage of up to 38.5 mg of granisetron hydrochloride injection has been reported without symptoms or only the occurrence of a slight headache.

11 DESCRIPTION

Granisetron hydrochloride injection, USP is a serotonin-3 (5-HT3) receptor antagonist. Chemically it is endo-N-(9-methyl-9-azabicyclo [3.3.1] non-3-yl)-1-methyl-1H-indazole-3-carboxamide hydrochloride with a molecular weight of 348.9 (312.4 free base). Its molecular formula is C18H24N4O•HCl, while its chemical structure is:

Granisetron hydrochloride USP is a white or almost white powder that is readily soluble in water and normal saline at 20°C. Granisetron hydrochloride injection, USP is a clear, colorless, sterile, nonpyrogenic, aqueous solution for intravenous administration.
Granisetron hydrochloride injection, USP 1 mg/mL is available in 1 mL single-dose and 4 mL multiple-dose vials.
Each mL contains 1.12 mg granisetron hydrochloride USP equivalent to granisetron 1 mg; sodium chloride, 9 mg; citric acid, 2 mg; methylparaben, 1.8 mg and propylparaben, 0.2 mg, as preservatives, water for injection, q.s., sodium hydroxide and hydrochloric acid, as pH adjusters. The solution's pH ranges from 4.0 to 6.0.

12 CLINICAL PHARMACOLOGY

12.1 Mechanism of Action

Granisetron is a selective 5-hydroxytryptamine3 (5-HT3) receptor antagonist with little or no affinity for other serotonin receptors, including 5-HT1; 5-HT1A; 5-HT1B/C; 5-HT2; for alpha1-, alpha2- or beta-adrenoreceptors; for dopamine-D2; or for histamine-H1; benzodiazepine; picrotoxin or opioid receptors.
Serotonin receptors of the 5-HT3 type are located peripherally on vagal nerve terminals and centrally in the chemoreceptor trigger zone of the area postrema. During chemotherapy-induced vomiting, mucosal enterochromaffin cells release serotonin, which stimulates 5-HT3 receptors. This evokes vagal afferent discharge and may induce vomiting. Animal studies demonstrate that, in binding to 5-HT3 receptors, granisetron blocks serotonin stimulation and subsequent vomiting after emetogenic stimuli such as cisplatin. In the ferret animal model, a single granisetron injection prevented vomiting due to high-dose cisplatin or arrested vomiting within 5 to 30 seconds.
In most human studies, granisetron has had little effect on blood pressure, heart rate or ECG. No evidence of an effect on plasma prolactin or aldosterone concentrations has been found in other studies.
Granisetron hydrochloride injection exhibited no effect on oro-cecal transit time in normal volunteers given a single intravenous infusion of 50 mcg/kg or 200 mcg/kg. Single and multiple oral doses slowed colonic transit in normal volunteers.

12.3 Pharmacokinetics

Chemotherapy-Induced Nausea and Vomiting
In adult cancer patients undergoing chemotherapy and in volunteers, mean pharmacokinetic data obtained from an infusion of a single 40 mcg/kg dose of granisetron hydrochloride injection are shown in Table 3.

Table 3 Pharmacokinetic Parameters in Adult Cancer Patients Undergoing Chemotherapy and in Volunteers, Following a Single Intravenous 40 mcg/kg Dose of Granisetron Hydrochloride Injection
 | Peak Plasma Concentration (ng/mL) | Terminal Phase Plasma Half-Life (h) | Total Clearance (L/h/kg) | Volume of Distribution (L/kg)
Cancer Patients
Mean Range | 63.8* 18 to 176 | 8.95* 0.9 to 31.1 | 0.38* 0.14 to 1.54 | 3.07* 0.85 to 10.4
Volunteers
21 to 42 years
Mean Range | 64.3† 11.2 to 182 | 4.91† 0.88 to 15.2 | 0.79† 0.2 to 2.56 | 3.04† 1.68 to 6.13
65 to 81 years
Mean Range | 57† 14.6 to 153 | 7.69† 2.65 to 17.7 | 0.44† 0.17 to 1.06 | 3.97† 1.75 to 7.01
* 5-minute infusion.
† 3-minute infusion.

Distribution
Plasma protein binding is approximately 65% and granisetron distributes freely between plasma and red blood cells.
Metabolism
Granisetron metabolism involves N-demethylation and aromatic ring oxidation followed by conjugation. In vitro liver microsomal studies show that granisetron’s major route of metabolism is inhibited by ketoconazole, suggestive of metabolism mediated by the cytochrome P-450 3A subfamily. Animal studies suggest that some of the metabolites may also have 5-HT3 receptor antagonist activity.
Elimination
Clearance is predominantly by hepatic metabolism. In normal volunteers, approximately 12% of the administered dose is eliminated unchanged in the urine in 48 hours. The remainder of the dose is excreted as metabolites, 49% in the urine, and 34% in the feces.
Subpopulations
Gender
There was high inter- and intra-subject variability noted in these studies. No difference in mean AUC was found between males and females, although males had a higher Cmax generally.
Elderly
The ranges of the pharmacokinetic parameters in elderly volunteers (mean age 71 years), given a single 40 mcg/kg intravenous dose of granisetron hydrochloride injection, were generally similar to those in younger healthy volunteers; mean values were lower for clearance and longer for half-life in the elderly patients (see Table 3).
Pediatric Patients
A pharmacokinetic study in pediatric cancer patients (2 to 16 years of age), given a single 40 mcg/kg intravenous dose of granisetron hydrochloride injection, showed that volume of distribution and total clearance increased with age. No relationship with age was observed for peak plasma concentration or terminal phase plasma half-life. When volume of distribution and total clearance are adjusted for body weight, the pharmacokinetics of granisetron are similar in pediatric and adult cancer patients.
Renal Failure Patients
Total clearance of granisetron was not affected in patients with severe renal failure who received a single 40 mcg/kg intravenous dose of granisetron hydrochloride injection.
Hepatically Impaired Patients
A pharmacokinetic study in patients with hepatic impairment due to neoplastic liver involvement showed that total clearance was approximately halved compared to patients without hepatic impairment. Given the wide variability in pharmacokinetic parameters noted in patients, dosage adjustment in patients with hepatic functional impairment is not necessary.
Postoperative Nausea and Vomiting
In adult patients (age range, 18 to 64 years) recovering from elective surgery and receiving general balanced anesthesia, mean pharmacokinetic data obtained from a single 1 mg dose of granisetron hydrochloride injection administered intravenously over 30 seconds are shown in Table 4.

Table 4 Pharmacokinetic Parameters in 16 Adult Surgical Patients Following a Single Intravenous 1 mg Dose of Granisetron Hydrochloride Injection
 | Terminal Phase Plasma Half-Life (h) | Total Clearance (L/h/kg) | Volume of Distribution (L/kg)
Mean | 8.63 | 0.28 | 2.42
Range | 1.77 to 17.73 | 0.07 to 0.71 | 0.71 to 4.13

The pharmacokinetics of granisetron in patients undergoing surgery were similar to those seen in cancer patients undergoing chemotherapy.

13 NONCLINICAL TOXICOLOGY

13.1 Carcinogenesis, Mutagenesis, Impairment of Fertility

In a 24-month carcinogenicity study, rats were treated orally with granisetron 1, 5 or 50 mg/kg/day (6, 30 or 300 mg/m^2/day). The 50 mg/kg/day dose was reduced to 25 mg/kg/day (150 mg/m^2/day) during week 59 due to toxicity. For a 50 kg person of average height (1.46 m^2 body surface area), these doses represent 16, 81 and 405 times the recommended clinical dose (0.37 mg/m^2, iv) on a body surface area basis. There was a statistically significant increase in the incidence of hepatocellular carcinomas and adenomas in males treated with 5 mg/kg/day (30 mg/m^2/day, 81 times the recommended human dose based on body surface area) and above, and in females treated with 25 mg/kg/day (150 mg/m^2/day, 405 times the recommended human dose based on body surface area). No increase in liver tumors was observed at a dose of 1 mg/kg/day (6 mg/m^2/day, 16 times the recommended human dose based on body surface area) in males and 5 mg/kg/day (30 mg/m^2/day, 81 times the recommended human dose based on body surface area) in females. In a 12-month oral toxicity study, treatment with granisetron 100 mg/kg/day (600 mg/m^2/day, 1622 times the recommended human dose based on body surface area) produced hepatocellular adenomas in male and female rats while no such tumors were found in the control rats. A 24-month mouse carcinogenicity study of granisetron did not show a statistically significant increase in tumor incidence, but the study was not conclusive.
Because of the tumor findings in rat studies, granisetron hydrochloride injection should be prescribed only at the dose and for the indication recommended [see Indications and Usage (1) and Dosage and Administration (2)].
Granisetron was not mutagenic in an in vitro Ames test and mouse lymphoma cell forward mutation assay, and in vivo mouse micronucleus test and in vitro and ex vivo rat hepatocyte UDS assays. It, however, produced a significant increase in UDS in HeLa cells in vitro and a significant increased incidence of cells with polyploidy in an in vitro human lymphocyte chromosomal aberration test.
Granisetron at subcutaneous doses up to 6 mg/kg/day (36 mg/m^2/day, 97 times the recommended human dose based on body surface area) was found to have no effect on fertility and reproductive performance of male and female rats.

14 CLINICAL STUDIES

14.1 Chemotherapy-Induced Nausea and Vomiting

Single-Day Chemotherapy
Cisplatin-Based Chemotherapy
In a double-blind, placebo-controlled study in 28 cancer patients, granisetron hydrochloride injection, administered as a single intravenous infusion of 40 mcg/kg, was significantly more effective than placebo in preventing nausea and vomiting induced by cisplatin chemotherapy (see Table 5).

Table 5 Prevention of Chemotherapy-Induced Nausea and Vomiting — Single-Day Cisplatin Therapy^1
 | Granisetron Hydrochloride Injection | Placebo | P-Value
Number of Patients | 14 | 14
Response Over 24 Hours
Complete Response^2 No Vomiting No More Than Mild Nausea | 93% 93% 93% | 7% 14% 7% | < 0.001 < 0.001 < 0.001
^1 Cisplatin administration began within 10 minutes of granisetron hydrochloride injection infusion and continued for 1.5 to 3 hours. Mean cisplatin dose was 86 mg/m^2 in the granisetron hydrochloride injection group and 80 mg/m^2 in the placebo group.
^2 No vomiting and no moderate or severe nausea.

Granisetron hydrochloride injection was also evaluated in a randomized dose response study of cancer patients receiving cisplatin ≥ 75 mg/m^2. Additional chemotherapeutic agents included: anthracyclines, carboplatin, cytostatic antibiotics, folic acid derivatives, methylhydrazine, nitrogen mustard analogs, podophyllotoxin derivatives, pyrimidine analogs, and vinca alkaloids. Granisetron hydrochloride injection doses of 10 and 40 mcg/kg were superior to 2 mcg/kg in preventing cisplatin-induced nausea and vomiting, but 40 mcg/kg was not significantly superior to 10 mcg/kg (see Table 6).

Table 6 Prevention of Chemotherapy-Induced Nausea and Vomiting — Single-Day High-Dose Cisplatin Therapy^1
 | Granisetron Hydrochloride Injection (mcg/kg) |  |  | P-Value (vs. 2 mcg/kg)
 | 2 | 10 | 40 | 10 | 40
Number of Patients | 52 | 52 | 53
Response Over 24 Hours
Complete Response^2 No Vomiting No More Than Mild Nausea | 31% 38% 58% | 62% 65% 75% | 68% 74% 79% | < 0.002 < 0.001 NS | < 0.001 < 0.001 0.007
^1 Cisplatin administration began within 10 minutes of granisetron hydrochloride injection infusion and continued for 2.6 hours (mean). Mean cisplatin doses were 96 to 99 mg/m^2.
^2 No vomiting and no moderate or severe nausea.

Granisetron hydrochloride injection was also evaluated in a double-blind, randomized dose response study of 353 patients stratified for high (≥ 80 to 120 mg/m^2) or low (50 to 79 mg/m^2) cisplatin dose. Response rates of patients for both cisplatin strata are given in Table 7.

Table 7 Prevention of Chemotherapy-Induced Nausea and Vomiting — Single-Day High-Dose and Low-Dose Cisplatin Therapy^1
 | Granisetron Hydrochloride Injection (mcg/kg) |  |  |  | P-Value (vs. 5 mcg/kg)
 | 5 | 10 | 20 | 40 | 10 | 20 | 40
High-Dose Cisplatin
Number of Patients | 40 | 49 | 48 | 47
Response Over 24 Hours
Complete Response^2 No Vomiting No Nausea | 18% 28% 15% | 41% 47% 35% | 40% 44% 38% | 47% 53% 43% | 0.018 NS 0.036 | 0.025 NS 0.019 | 0.004 0.016 0.005
Low-Dose Cisplatin
Number of Patients | 42 | 41 | 40 | 46
Response Over 24 Hours
Complete Response^2 No Vomiting No Nausea | 29% 36% 29% | 56% 63% 56% | 58% 65% 38% | 41% 43% 33% | 0.012 0.012 0.012 | 0.009 0.008 NS | NS NS NS
^1 Cisplatin administration began within 10 minutes of granisetron hydrochloride injection infusion and continued for 2 hours (mean). Mean cisplatin doses were 64 and 98 mg/m^2 for low and high strata.
^2 No vomiting and no use of rescue antiemetic.

For both the low and high cisplatin strata, the 10, 20, and 40 mcg/kg doses were more effective than the 5 mcg/kg dose in preventing nausea and vomiting within 24 hours of chemotherapy administration. The 10 mcg/kg dose was at least as effective as the higher doses.
Moderately Emetogenic Chemotherapy
Granisetron hydrochloride injection, 40 mcg/kg, was compared with the combination of chlorpromazine (50 to 200 mg/24 hours) and dexamethasone (12 mg) in patients treated with moderately emetogenic chemotherapy, including primarily carboplatin > 300 mg/m^2, cisplatin 20 to 50 mg/m^2 and cyclophosphamide > 600 mg/m^2. Granisetron hydrochloride injection was superior to the chlorpromazine regimen in preventing nausea and vomiting (see Table 8).

Table 8 Prevention of Chemotherapy-Induced Nausea and Vomiting—Single-Day Moderately Emetogenic Chemotherapy
 | Granisetron Hydrochloride Injection | Chlorpromazine^1 | P-Value
Number of Patients | 133 | 133
Response Over 24 Hours
Complete Response^2 No Vomiting No More Than Mild Nausea | 68% 73% 77% | 47% 53% 59% | < 0.001 < 0.001 < 0.001
^1 Patients also received dexamethasone, 12 mg.
^2 No vomiting and no moderate or severe nausea.

In other studies of moderately emetogenic chemotherapy, no significant difference in efficacy was found between granisetron hydrochloride doses of 40 mcg/kg and 160 mcg/kg.
Repeat-Cycle Chemotherapy
In an uncontrolled trial, 512 cancer patients received granisetron hydrochloride injection, 40 mcg/kg, prophylactically, for two cycles of chemotherapy, 224 patients received it for at least four cycles, and 108 patients received it for at least six cycles. Granisetron hydrochloride injection efficacy remained relatively constant over the first six repeat cycles, with complete response rates (no vomiting and no moderate or severe nausea in 24 hours) of 60% to 69%. No patients were studied for more than 15 cycles.
Pediatric Studies
A randomized double-blind study evaluated the 24-hour response of 80 pediatric cancer patients (age 2 to 16 years) to granisetron hydrochloride injection 10, 20 or 40 mcg/kg. Patients were treated with cisplatin ≥ 60 mg/m^2, cytarabine ≥ 3 g/m^2, cyclophosphamide ≥ 1 g/m^2 or nitrogen mustard ≥ 6 mg/m^2 (see Table 9).

Table 9 Prevention of Chemotherapy-Induced Nausea and Vomiting in Pediatric Patients
 | Granisetron Hydrochloride Injection Dose (mcg/kg)
 | 10 | 20 | 40
Number of Patients Median Number of Vomiting Episodes Complete Response Over 24 Hours^1 | 29 2 21% | 26 3 31% | 25 1 32%
^1 No vomiting and no moderate or severe nausea.

A second pediatric study compared granisetron hydrochloride injection 20 mcg/kg to chlorpromazine plus dexamethasone in 88 patients treated with ifosfamide ≥ 3 g/m^2/day for two or three days. Granisetron hydrochloride injection was administered on each day of ifosfamide treatment. At 24 hours, 22% of granisetron hydrochloride injection patients achieved complete response (no vomiting and no moderate or severe nausea in 24 hours) compared with 10% on the chlorpromazine regimen. The median number of vomiting episodes with granisetron hydrochloride injection was 1.5; with chlorpromazine it was 7.

14.2 Postoperative Nausea and Vomiting

Prevention of Postoperative Nausea and Vomiting
The efficacy of granisetron hydrochloride injection for prevention of postoperative nausea and vomiting was evaluated in 868 patients, of which 833 were women, 35 men, 484 Caucasians, 348 Asians, 18 Blacks, 18 Other, with 61 patients 65 years or older. Granisetron hydrochloride injection was evaluated in two randomized, double-blind, placebo-controlled studies in patients who underwent elective gynecological surgery or cholecystectomy and received general anesthesia. Patients received a single intravenous dose of granisetron hydrochloride injection (0.1 mg, 1 mg or 3 mg) or placebo either 5 minutes before induction of anesthesia or immediately before reversal of anesthesia. The primary endpoint was the proportion of patients with no vomiting for 24 hours after surgery. Episodes of nausea and vomiting and use of rescue antiemetic therapy were recorded for 24 hours after surgery. In both studies, granisetron hydrochloride injection (1 mg) was more effective than placebo in preventing postoperative nausea and vomiting (see Table 10). No additional benefit was seen in patients who received the 3 mg dose.

Table 10 Prevention of Postoperative Nausea and Vomiting in Adult Patients
Study and Efficacy Endpoint | Placebo | Granisetron Hydrochloride Injection 0.1 mg | Granisetron Hydrochloride Injection 1 mg | Granisetron Hydrochloride Injection 3 mg
Study 1
Number of Patients | 133 | 132 | 134 | 128
No Vomiting
0 to 24 hours | 34% | 45% | 63%** | 62%**
No Nausea
0 to 24 hours | 22% | 28% | 50%** | 42%**
No Nausea or Vomiting
0 to 24 hours | 18% | 27% | 49%** | 42%**
No Use of Rescue Antiemetic Therapy
0 to 24 hours | 60% | 67% | 75%* | 77%*
Study 2
Number of Patients | 117 | – | 110 | 114
No Vomiting
0 to 24 hours | 56% | – | 77%** | 75%*
No Nausea
0 to 24 hours | 37% | – | 59%** | 56%*
*P<0.05
**P<0.001 versus placebo
Note: No Vomiting = no vomiting and no use of rescue antiemetic therapy; No Nausea = no nausea and no use of rescue antiemetic therapy

Gender/Race
There were too few male and Black patients to adequately assess differences in effect in either population.
Treatment of Postoperative Nausea and Vomiting
The efficacy of granisetron hydrochloride injection for treatment of postoperative nausea and vomiting was evaluated in 844 patients, of which 731 were women, 113 men, 777 Caucasians, 6 Asians, 41 Blacks, 20 Other, with 107 patients 65 years or older. Granisetron hydrochloride injection was evaluated in two randomized, double-blind, placebo-controlled studies of adult surgical patients who received general anesthesia with no prophylactic antiemetic agent, and who experienced nausea or vomiting within 4 hours postoperatively. Patients received a single intravenous dose of granisetron hydrochloride injection (0.1 mg, 1 mg or 3 mg) or placebo after experiencing postoperative nausea or vomiting. Episodes of nausea and vomiting and use of rescue antiemetic therapy were recorded for 24 hours after administration of study medication. Granisetron hydrochloride injection was more effective than placebo in treating postoperative nausea and vomiting (see Table 11). No additional benefit was seen in patients who received the 3 mg dose.

Table 11 Treatment of Postoperative Nausea and Vomiting in Adult Patients
Study and Efficacy Endpoint | Placebo | Granisetron Hydrochloride Injection 0.1 mg | Granisetron Hydrochloride Injection 1 mg | Granisetron Hydrochloride Injection 3 mg
Study 3
Number of Patients | 133 | 128 | 133 | 125
No Vomiting
0 to 6 hours | 26% | 53%*** | 58%*** | 60%***
0 to 24 hours | 20% | 38%*** | 46%*** | 49%***
No Nausea
0 to 6 hours | 17% | 40%*** | 41%*** | 42%***
0 to 24 hours | 13% | 27%** | 30%** | 37%***
No Use of Rescue Antiemetic Therapy
0 to 6 hours | – | – | – | –
0 to 24 hours | 33% | 51%** | 61%*** | 61%***
Study 4
Number of Patients (All Patients) | 162 | 163 | – | –
No Vomiting
0 to 6 hours | 20% | 32%* | – | –
0 to 24 hours | 14% | 23%* | – | –
No Nausea
0 to 6 hours | 13% | 18% | – | –
0 to 24 hours | 9% | 14% | – | –
No Nausea or Vomiting
0 to 6 hours | 13% | 18% | – | –
0 to 24 hours | 9% | 14% | – | –
No Use of Rescue Antiemetic Therapy
0 to 6 hours | – | – | – | –
0 to 24 hours | 24% | 34%* | –
Number of Patients (Treated for Vomiting)^1 | 86 | 103 | – | –
No Vomiting
0 to 6 hours | 21% | 27% | – | –
0 to 24 hours | 14% | 20% | – | –
*P<0.05
**P<0.01
***P<0.001 versus placebo
1 Protocol Specified Analysis: Patients who had vomiting prior to treatment
Note: No vomiting = no vomiting and no use of rescue antiemetic therapy; No nausea = no nausea and no use of rescue antiemetic therapy

Gender/Race
There were too few male and Black patients to adequately assess differences in effect in either population.

16 HOW SUPPLIED/STORAGE AND HANDLING

Granisetron hydrochloride injection USP, 1 mg/mL (free base), is supplied in 1 mL Single-Dose Vials and 4 mg/4 mL Multiple-Dose Vials.
1 mg (base) per mL:
Single-Dose Vials in a carton of 1 NDC 55150-175-01
4 mg per 4 mL (1 mg (base)/mL):
Multiple-Dose Vials in a carton of 1 NDC 55150-176-04
Store at 20° to 25°C (68° to 77°F) [see USP Controlled Room Temperature].
Discard unused portion for the single-dose vials.
Once the multiple-dose vial is penetrated, its contents should be used within 30 days.
Do not freeze. Protect from light. Retain in carton until time of use.
The vial stopper is not made with natural rubber latex.

17 PATIENT COUNSELING INFORMATION

Patients should be informed that the most common adverse reactions for the indication of chemotherapy induced nausea and vomiting are headache and constipation (see Table 1).
Patients should be informed that the most common adverse reactions for the indication of postoperative nausea and vomiting are pain, headache, fever, abdominal pain and hepatic enzyme increased (see Table 2).
Patients should be advised of the risk of allergic reactions if they have a prior allergic reaction to a class of antiemetics known as 5-HT3 receptor antagonists.
Electrocardiogram changes (QT prolongation) have been reported with the use of granisetron hydrochloride. Patients should be cautioned about the use of this drug if they have heart problems or take medications for heart problems.

17.1 Serotonin Syndrome

Advise patients of the possibility of serotonin syndrome with concomitant use of granisetron and another serotonergic agent such as medications to treat depression and migraines. Advise patients to seek immediate medical attention if the following symptoms occur: changes in mental status, autonomic instability, neuromuscular symptoms with or without gastrointestinal symptoms.
Distributed by:
Eugia US LLC
279 Princeton-Hightstown Rd.
E. Windsor, NJ 08520
Manufactured by:
Eugia Pharma Specialities Limited
Hyderabad - 500032
India

PACKAGE LABEL-PRINCIPAL DISPLAY PANEL - 1 mg (base) per mL - 1 mL Container Label

Rx only NDC 55150-175-01
Granisetron
Hydrochloride
Injection, USP
1 mg (base) per mL
For Intravenous
use only
1 mL Single-Dose Vial

PACKAGE LABEL-PRINCIPAL DISPLAY PANEL - 1 mg (base) per mL - Container-Carton [1 Vial]

Rx only NDC 55150-175-01
Granisetron
Hydrochloride
Injection, USP
1 mg (base) per mL
For Intravenous use only
Sterile
1 mL Single-Dose Vial
eugia

PACKAGE LABEL-PRINCIPAL DISPLAY PANEL - 4 mg per 4 mL (1 mg (base)/mL) - 4 mL Container Label

Rx only NDC 55150-176-04
Granisetron
Hydrochloride
Injection, USP
4 mg per 4 mL
(1 mg (base)/mL)
For Intravenous
use only
4 mL Multiple-Dose Vial

PACKAGE LABEL-PRINCIPAL DISPLAY PANEL - 4 mg per 4 mL (1 mg (base)/mL) - Container-Carton [1 Vial]

Rx only NDC 55150-176-04
Granisetron
Hydrochloride
Injection, USP
4 mg per 4 mL
(1 mg (base)/mL)
For Intravenous use only
Sterile
4 mL Multiple-Dose Vial
eugia